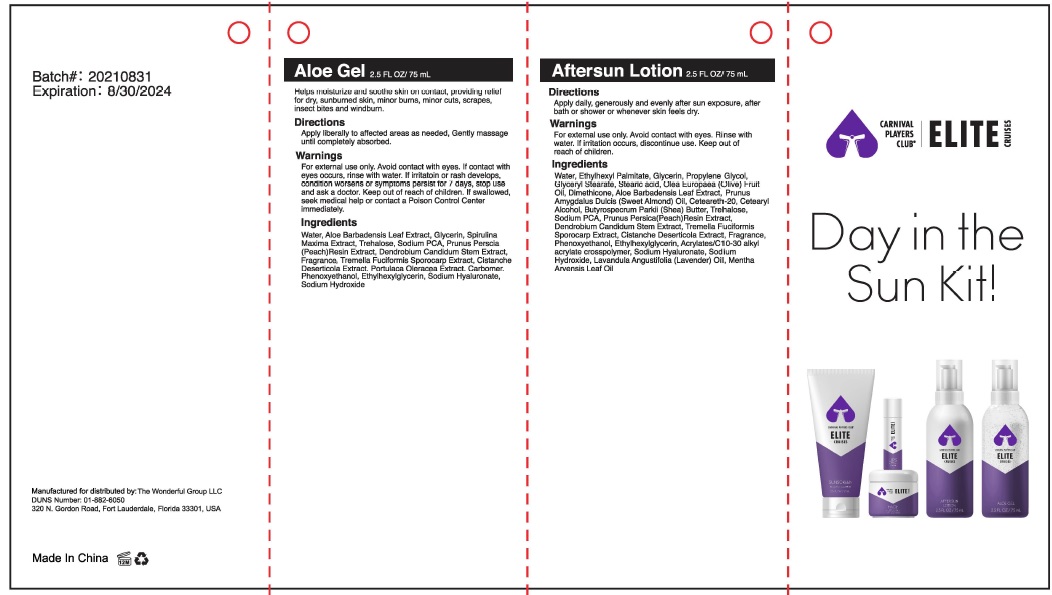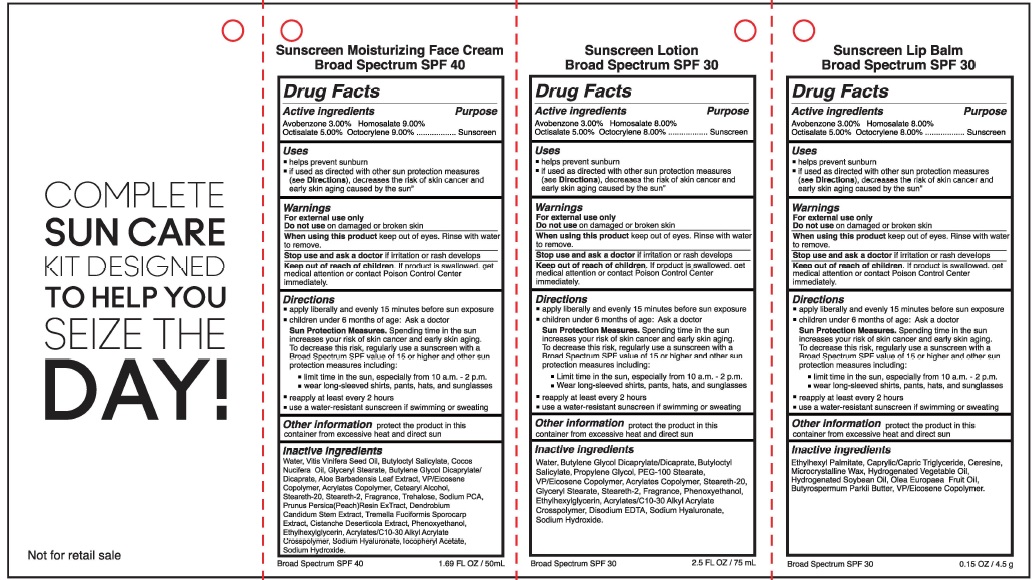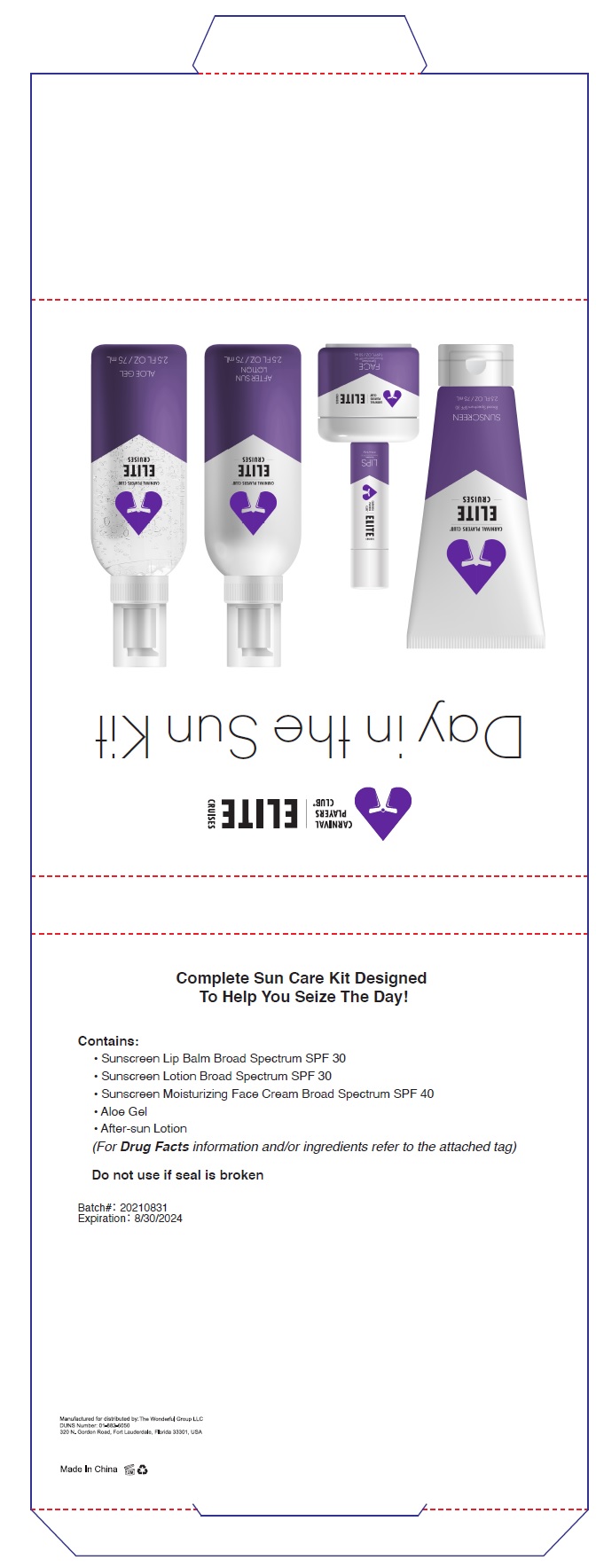 DRUG LABEL: Day in the sun kit
NDC: 80782-001 | Form: KIT | Route: TOPICAL
Manufacturer: THE WONDERFUL GROUP LLC
Category: otc | Type: HUMAN OTC DRUG LABEL
Date: 20230124

ACTIVE INGREDIENTS: AVOBENZONE 3 g/100 mL; HOMOSALATE 8 g/100 mL; OCTISALATE 5 g/100 mL; OCTOCRYLENE 8 g/100 mL; AVOBENZONE 3 g/100 mL; HOMOSALATE 9 g/100 mL; OCTISALATE 5 g/100 mL; OCTOCRYLENE 9 g/100 mL; AVOBENZONE 3 g/100 g; HOMOSALATE 9 g/100 g; OCTISALATE 5 g/100 g; OCTOCRYLENE 9 g/100 g
INACTIVE INGREDIENTS: WATER; BUTYLENE GLYCOL DICAPRYLATE/DICAPRATE; BUTYLOCTYL SALICYLATE; PROPYLENE GLYCOL; PEG-100 STEARATE; VINYLPYRROLIDONE/EICOSENE COPOLYMER; BUTYL ACRYLATE/METHYL METHACRYLATE/METHACRYLIC ACID COPOLYMER (18000 MW); STEARETH-20; GLYCERYL MONOSTEARATE; STEARETH-2; PHENOXYETHANOL; ETHYLHEXYLGLYCERIN; CARBOMER INTERPOLYMER TYPE A (ALLYL SUCROSE CROSSLINKED); EDETATE DISODIUM ANHYDROUS; HYALURONATE SODIUM; SODIUM HYDROXIDE; WATER; GRAPE SEED OIL; BUTYLOCTYL SALICYLATE; COCONUT OIL; GLYCERYL MONOSTEARATE; ALOE VERA LEAF; VINYLPYRROLIDONE/EICOSENE COPOLYMER; CETOSTEARYL ALCOHOL; TREHALOSE; SODIUM PYRROLIDONE CARBOXYLATE; PRUNUS PERSICA TWIG; DENDROBIUM MONILIFORME WHOLE; TREMELLA FUCIFORMIS FRUITING BODY; CISTANCHE DESERTICOLA STEM; PHENOXYETHANOL; ETHYLHEXYLGLYCERIN; CARBOMER INTERPOLYMER TYPE A (ALLYL SUCROSE CROSSLINKED); HYALURONATE SODIUM; .ALPHA.-TOCOPHEROL ACETATE; BUTYLENE GLYCOL DICAPRYLATE/DICAPRATE; BUTYL ACRYLATE/METHYL METHACRYLATE/METHACRYLIC ACID COPOLYMER (18000 MW); STEARETH-20; STEARETH-2; SODIUM HYDROXIDE; ETHYLHEXYL PALMITATE; MEDIUM-CHAIN TRIGLYCERIDES; SODIUM DICHLOROACETATE; MICROCRYSTALLINE WAX; CANOLA OIL; HYDROGENATED SOYBEAN OIL; OLIVE OIL; BUTYROSPERMUM PARKII (SHEA) BUTTER UNSAPONIFIABLES; VINYLPYRROLIDONE/EICOSENE COPOLYMER

Active ingredients

Avobenzone 3.0% Homosalate 8.0%
Octisalate 5.0% Octocrylene 8.0%

Purpose

Sunscreen

Uses

helps prevent sunburn
if used as directed with other sun protection measures (see Directions), decreases the risk of skin cancer and early skin aging caused by the sun

Warnings

For external use only
Do not use on damaged or broken skin
When using this product, keep out of eyes. Rinse with water to remove.
Stop use and ask a doctor if irritation or rash develops
Keep out of reach of children. If product is swallowed, get medical attention or contact Poison Control Center immediately.

Directions

apply liberally and evenly 15 minutes before sun exposure
children under 6 months of age: Ask a doctor
Sun Protection Measures. Spending time in the sun increases your risk of skin cancer and early skin aging.
To decrease this risk, regularly use a sunscreen with a Broad Spectrum SPF value of 15 or higher and other sun protection measures including:

- limit time in the sun, especially from 10 a.m. - 2 p.m.
- wear long-sleeved shirts, pants, hats, and sunglasses
- reapply at least every 2 hours
- use a water-resistant sunscreen if swimming or sweating

Other information

protect the product in this container from excessive heat and direct sun

Inactive ingredients

Water, Butylene Glycol Dicaprylate/Dicaprate, Butyloctyl Salicylate, Propylene Glycol, PEG-100 Stearate,VP/Eicosene Copolymer, Acrylates Copolymer, Steareth-20,Glyceryl Stearate, Steareth-2, Fragrance, Phenoxyethanol,Ethylhexylglycerin, Acrylates/C1 0-30 Alkyl Acrylate
Crosspolymer, Disodium EDTA, Sodium Hyaluronate,Sodium Hydroxide,fragrance

Active ingredients

Avobenzone 3.00% Homosalate 9.0%
Octisalate 5.0% Octocrylene 9.0%

Purpose

Sunscreen

Uses

helps prevent sunburn
if used as directed with other sun protection measures (see Directions), decreases the risk of skin cancer and early skin aging caused by the sun”

Warnings

For external use only
Do not use on damaged or broken skin
When using this product, keep out of eyes. Rinse with water to remove.
Stop use and ask a doctor if irritation or rash develops
Keep out of reach of children. If a product is swallowed, get medical attention or contact a Poison Control Center immediately.

Directions

apply liberally and evenly 15 minutes before sun exposure
children under 6 months of age: Ask a doctor
Sun Protection Measures. Spending time in the sun increases your risk of skin cancer and early skin aging.
To decrease this risk, regularly use a sunscreen with a Broad Spectrum SPF value of 15 or higher and other sun protection measures including:

- Limit time in the sun, especially from 10 a.m. - 2 p.m.
- Wear long-sleeved shirts, pants, hats, and sunglasses
- reapply at least every 2 hours
- use a water-resistant sunscreen if swimming or sweating

Other information

protect the product in this container from excessive heat and direct sun

Inactive ingredients

Water, Vilis Vinifara Seed Oil, Butyloctyl Salicylate, Cocos Nucifera Oil, Glyceryl Stearate, Butylene Glycol Dicaprylate/Dicaprate, Aloe Barbadensis Leaf Extract, VP/Eicosene Copolymer, Acrylates Copolymer, Cetearyl Alcohol,Steareth-20, Steareth-2, Fragrance, Trehalose, Sodium PCA,Prunus Persica(Peach)Resin ExTract, DendrobiumCandidum Stem Extract, Tremella Fuciformis Sporocarp Extract, Cistanche Deserticola Extract, Phenoxyethanol,Ethylhexylglycerin, Acrylates/C10-30 Alkyl Acrylate Crosspolymer, Sodium Hyaluronate,TocopheryiAcetate,Sodium Hydroxide,fragrance

Active ingredients

Avobenzone 3.0% Homosalate 8.0%
Octisalate 5.0% Octocrylene 8.0%

Purpose

Sunscreen

Uses

helps prevent sunburn
if used as directed with other sun protection measures (see Directions), decreases the risk of skin cancer and early skin aging caused by the sun

Warnings

For external use only
Do not use on damaged or broken skin
When using this product, keep out of eyes. Rinse with water to remove.
Stop use and ask a doctor if irritation or rash develops
Keep out of reach of children. If product is swallowed, get medical attention or contact Poison Control Center immediately.

Directions

apply liberally and evenly 15 minutes before sun exposure
children under 6 months of age: Ask a doctor
Sun Protection Measures. Spending time in the sun increases your risk of skin cancer and early skin aging.
To decrease this risk, regularly use a sunscreen with a Broad Spectrum SPF value of 15 or higher and other sun protection measures including:

- limit time in the sun, especially from 10 a.m. - 2 p.m.
- wear long-sleeved shirts, pants, hats, and sunglasses
- reapply at least every 2 hours
- use a water-resistant sunscreen if swimming or sweating

Other information

protect the product in this container from excessive heat and direct sun

Inactive ingredients

Ethylhexyl Palmitate, Caprylic/Capric Triglyceride, Ceresine,Microcrystalline Wax, Hydrogenated Vegetable Oil,Hydrogenated Soybean Oil, Olea Europaea Fruit Oil,Butyrospermum Parkii Butter, VP/Eicosene Copolymer,fragrance